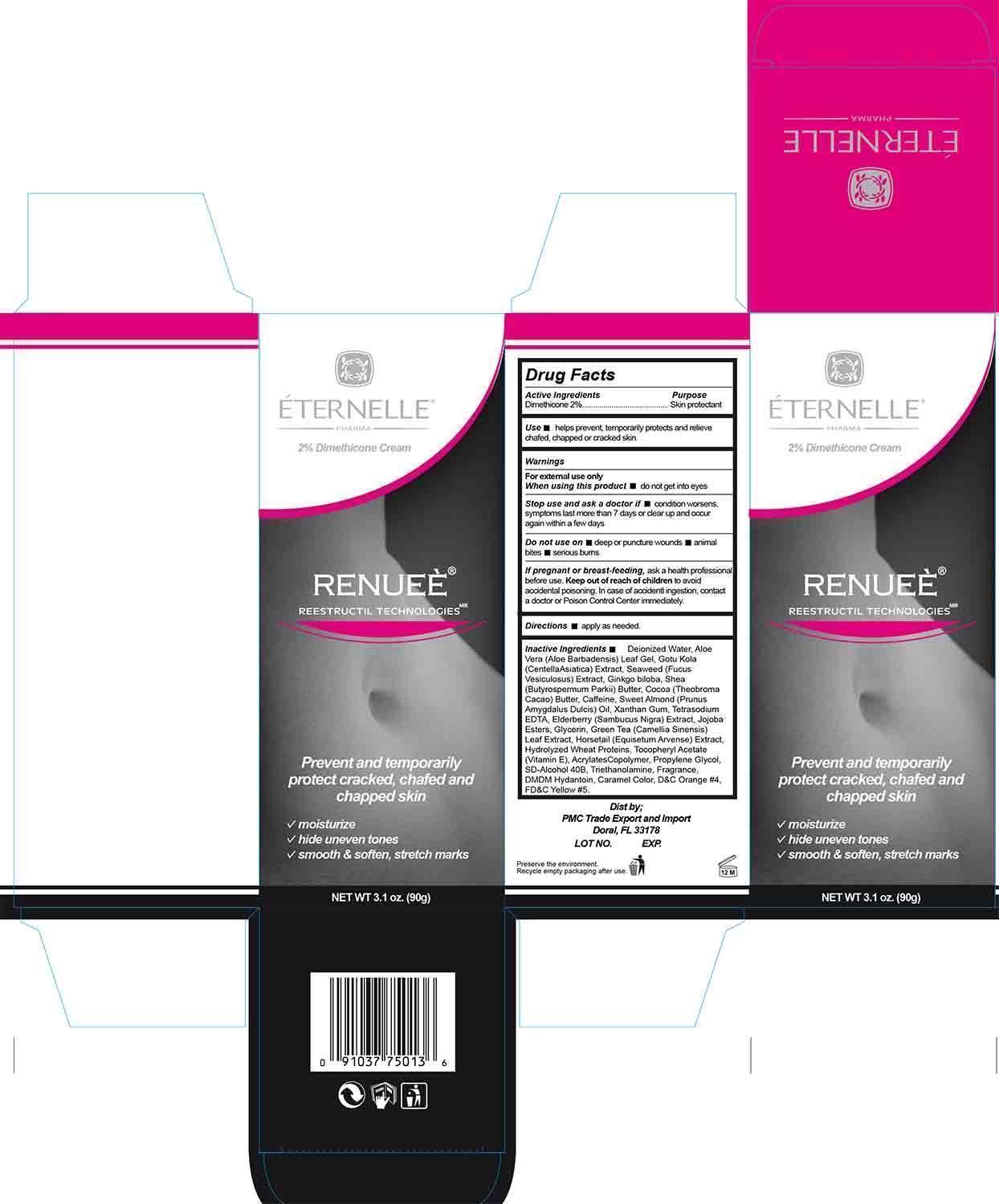 DRUG LABEL: Renuee
NDC: 68973-002 | Form: CREAM
Manufacturer: PMC TRADE, EXPORT AND IMPORT 
Category: otc | Type: HUMAN OTC DRUG LABEL
Date: 20140729

ACTIVE INGREDIENTS: DIMETHICONE 2 g/100 g
INACTIVE INGREDIENTS: WATER; ALOE VERA LEAF; CENTELLA ASIATICA; FUCUS VESICULOSUS; GINKGO BILOBA WHOLE; SHEA BUTTER; CAFFEINE; ALMOND OIL; XANTHAN GUM; EDETATE SODIUM; SAMBUCUS NIGRA FLOWERING TOP; JOJOBA OIL, RANDOMIZED; GLYCERIN; GREEN TEA LEAF; EQUISETUM ARVENSE BRANCH; HYDROLYZED WHEAT PROTEIN (ENZYMATIC, 3000 MW); ALPHA-TOCOPHEROL ACETATE; PROPYLENE GLYCOL; TROLAMINE; DMDM HYDANTOIN; D&C ORANGE NO. 11; FD&C YELLOW NO. 5

DRUG FACTS

Active Ingredient

Dimethicone 2%

Purpose

Skin protectant

Use

■ helps prevent, temporarily protects and relieve chafed, chapped, or cracked skin

Warnings

For external use only

When using this product

■ do not get into eyes

Stop use and ask a doctor if

■ condition worsens, symptoms last more than 7 days or clear up and occur again within a few days.

Do not use on

■ deep or puncture wounds ■ animal bites ■ serious burns

If pregnant or breast feeding

ask a health professional before use

Keep out of reach of children

to avoid accidental poisoning, in case of accidental ingestion contact a doctor or Poison Control Center immediately.

Directions

apply as needed

Inactive Ingredients

Deionized Water, Aloe Vera (Aloe Barbadensis) Leaf Gel, Gotu Kola (Centella Asiatica) Extract, Seaweed (Fucus Vesiculosus) Extract, Ginkgo biloba, Shea (Butyrospermum Parkii) Butter, Cocoa (Theobroma Cacao) Butter, Caffeine, Sweet Almond (Prunus Amygdalus Dulcis) Oil, Xanthan Gum, Tetrasodium EDTA, Elderberry (Sambucus Nigra) Extract, Jojoba Esters, Glycerin, Green Tea (Camellia Sinensis) Leaf Extract, Horsetail (Equisetum Arvense) Extract, Hydrolyzed Wheat Proteins, Tocopheryl Acetate (Vitamin E), Acrylates Copolymer, Propylene Glycol, SD-Alcohol 40B, Triethanolamine, Fragrance, DMDM Hydantoin, Caramel Color, D&C Orange #4, FD&C Yellow #5